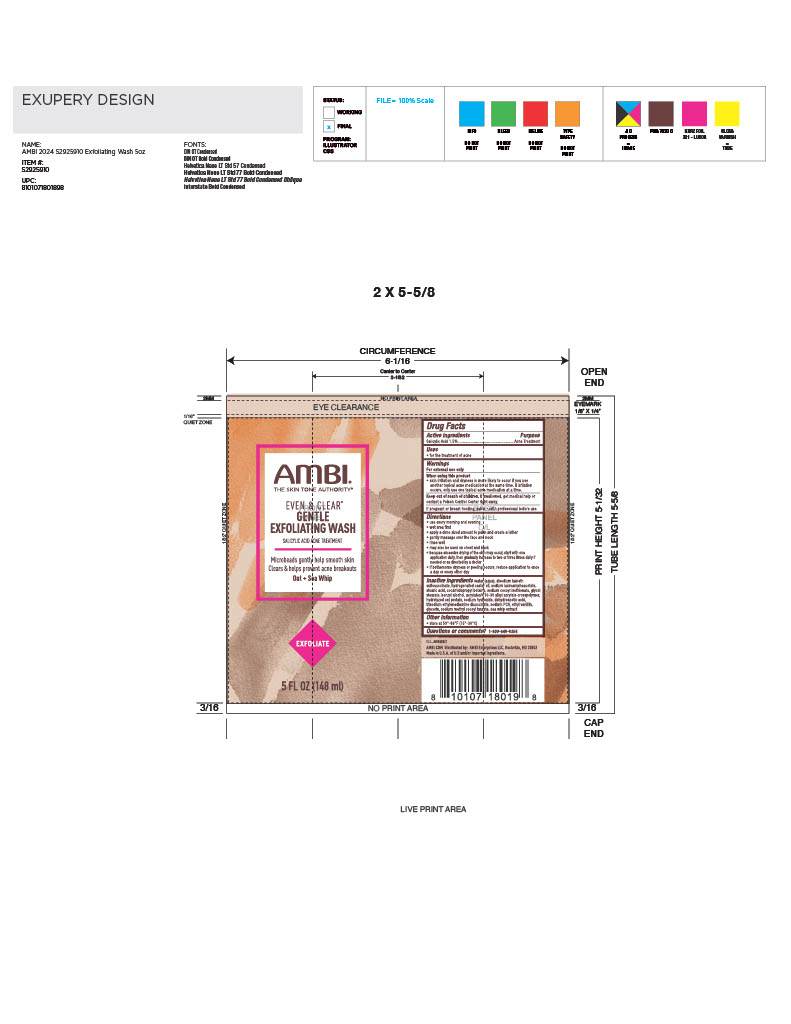 DRUG LABEL: Even and Clear Exfoliating Wash
NDC: 73453-113 | Form: LIQUID
Manufacturer: Ambi Enterprises, LLC
Category: otc | Type: HUMAN OTC DRUG LABEL
Date: 20260130

ACTIVE INGREDIENTS: SALICYLIC ACID 15 mg/1 mL
INACTIVE INGREDIENTS: SODIUM COCOYL ISETHIONATE; HYDROGENATED CASTOR OIL; GLYCOL STEARATE; ETHYL VANILLIN; GLYCERIN; DISODIUM LAURETH SULFOSUCCINATE; SODIUM LAUROAMPHOACETATE; WATER; DEEPSEA WHIPTAIL; ACRYLATES/C10-30 ALKYL ACRYLATE CROSSPOLYMER (60000 MPA.S); SODIUM PCA; SODIUM HYDROXIDE; DEHYDROACETIC ACID; SODIUM METHYL COCOYL TAURATE; STEARIC ACID; COCAMIDOPROPYL BETAINE; BENZYL ALCOHOL; OAT AMINO ACIDS; TRISODIUM ETHYLENEDIAMINE DISUCCINATE

Even and Clear Gentle Exfoliating Wash

Active ingredients

Salicylic Acid 1.5%

Purpose

Acne Treatment

Uses

for the treatment of acne

Warnings

For external use only

When using this product

skin irritation and dryness is more likely to occur if you use another topical acne medication at the same time. If irritation occurs, only use one topical acne medication at a time.

Keep out of reach of children

If swallowed, get medical help or contact a Poison Control Center right away.

If pregant or breastfeeding

If pregnant or breastfeeding ask a health professional before use

Directions

- use every morning and evening
- wet area first
- apply a dime sized amount to palm and create a lather
- gently massage over the face and neck
- rinse well
- may also be used on chest and back
- because excessive drying of the skin may occur, start with one application daily, then gradually increase to two or three times daily if needed or as directed by a doctor.
- if bothersome dryness or peeling occurs, reduce application to once a day or every other day

Inactive ingredients

Water (Aqua), Disodium Laureth Sulfosuccinate, Hydrogenated Castor Oil, Sodium Lauroamphoacetate, Stearic Acid, Cocamidopropyl Betaine, Sodium Cocoyl Isethionate, Glycol Stearate, Benzyl Alcohol, Acrylates/C10-30 Alkyl Acrylate Crosspolymer, Hydrolyzed Oat Protein, Sodium Hydroxide, Dehydroacetic Acid, Trisodium Ethylenediamine Disuccinate, Sodium PCA, Ethyl Vanillin, Glycerin, Sodium Methyl Cocoyl Taurate, Sea Whip Extract

Other information

store at 59-86 degrees F (15-30 degrees C)

Questions or comments?

1-800-946-6354